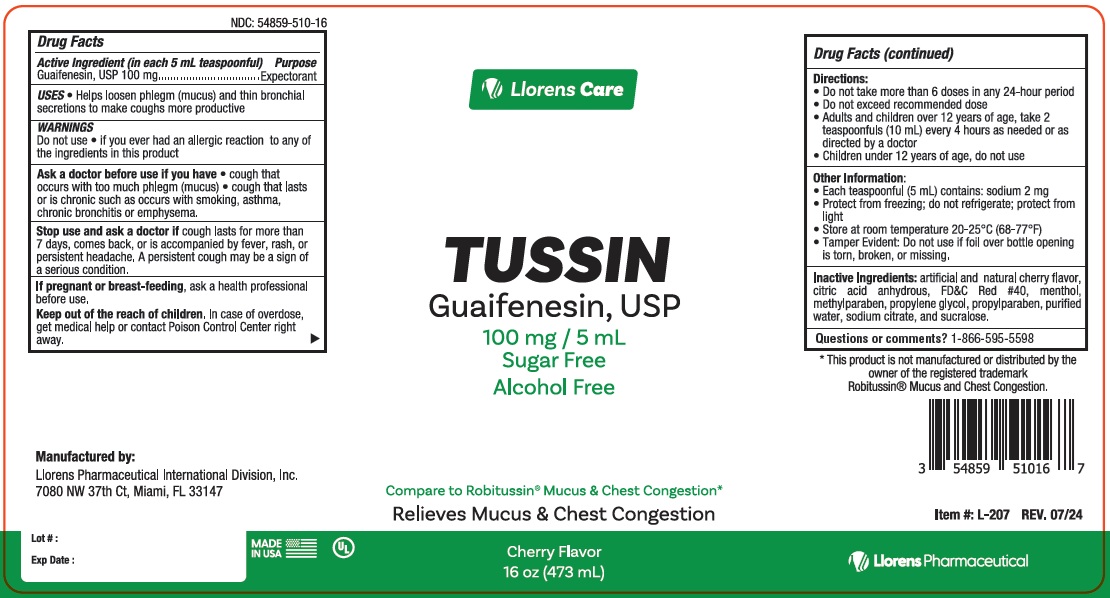 DRUG LABEL: Llorens Care Tussin
NDC: 54859-510 | Form: LIQUID
Manufacturer: Llorens Pharmaceutical International Division, Inc.
Category: otc | Type: HUMAN OTC DRUG LABEL
Date: 20251231

ACTIVE INGREDIENTS: GUAIFENESIN 100 mg/5 mL
INACTIVE INGREDIENTS: ANHYDROUS CITRIC ACID; FD&C RED NO. 40; MENTHOL; METHYLPARABEN; PROPYLENE GLYCOL; PROPYLPARABEN; WATER; SODIUM CITRATE; SUCRALOSE

LlorensCare Tussin 510

ACTIVE INGREDIENT

In each 5 mL teaspoonful

Guaifenesin - 100 mg

Purpose

Expectorant

Uses

- helps loosen phlegm (mucus) and thin bronchial secretions to make coughs more productive

Warnings

Do not use

- if you ever had an allergic reaction to any of the ingredients in this product

Ask a doctor before use if you have

- cough that occurs with too much phlegm (mucus)
- cough that lasts or is chronic such as occurs with smoking, asthma, chronic bronchitis, or emphysema

Stop use and ask a doctor if cough lasts more than 7 days, comes back or is accompanied by fever, rash, or persistent headache. These could be signs of a serious condition.

PREGNANCY OR BREAST FEEDING

If pregnant or breast-feeding,ask a health professional before use.

Keep out of reach of children. In case of overdose, get medical help or contact a Poison Control Center right away

Directions

- do not take more than 6 doses in a 24 hour period
- do not exceed recommended dose

adults and children 12 years and over | 2 teaspoonfuls (10 mL) every 4 hours as needed or as directed by a doctor
children under 12 years | do not use

INACTIVE INGREDIENT

Inactive ingredients: artificial and natural cherry flavor, citric acid, FD&C red #40, menthol, methylparaben, propylene glycol, propylparaben, purified water, sodium citrate, sucralose

Questions or comments? 1-866-595-5598

RECENT MAJOR CHANGES

typo